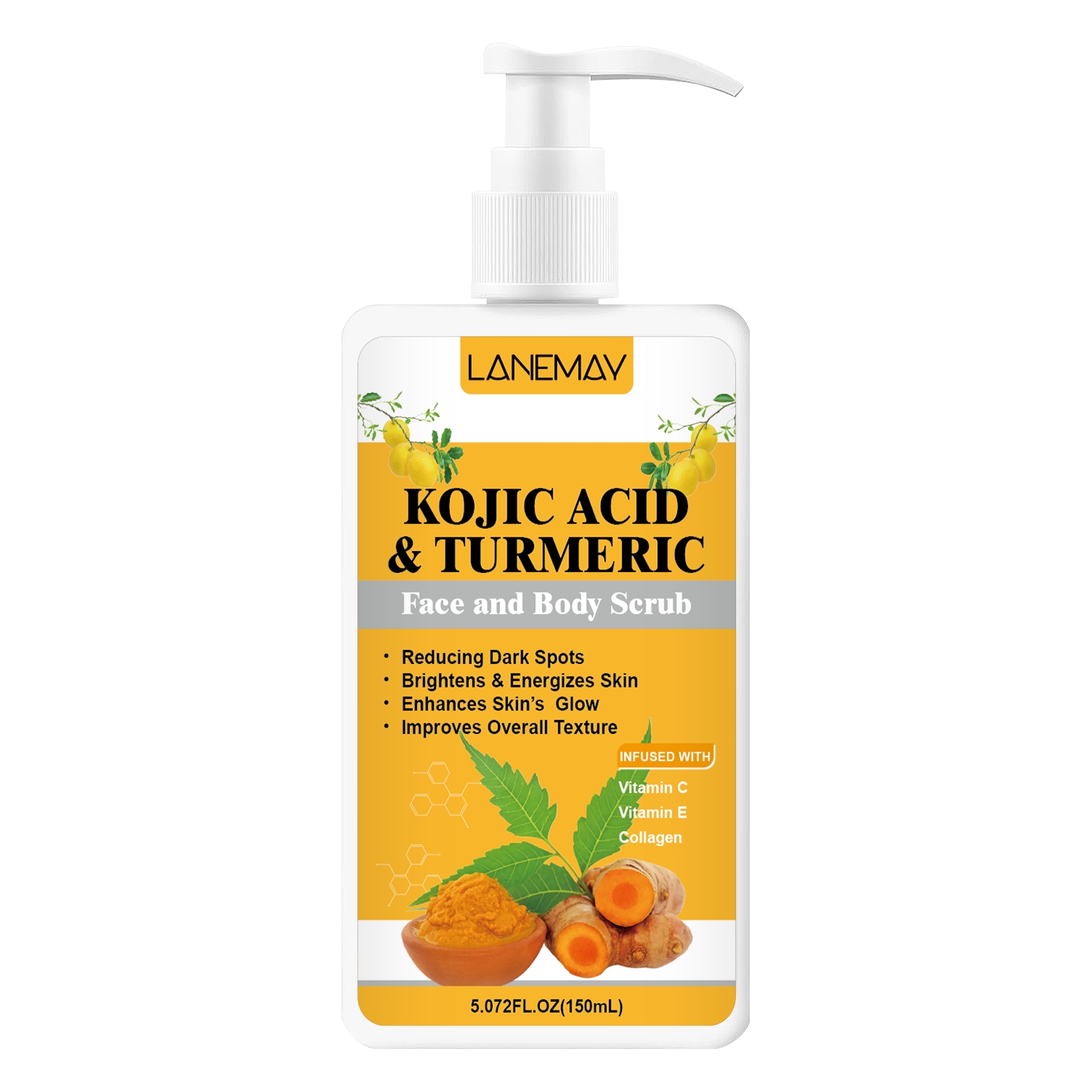 DRUG LABEL: Kojic Acid Turmeric Face and Body Scrub
NDC: 84025-224 | Form: CREAM
Manufacturer: Guangzhou Yanxi Biotechnology Co., Ltd
Category: otc | Type: HUMAN OTC DRUG LABEL
Date: 20241021

ACTIVE INGREDIENTS: GLYCERIN 5 mg/150 mL; SORBITOL 7 mg/150 mL
INACTIVE INGREDIENTS: WATER

DOSAGE AND ADMINISTRATION

Wet your skin,take a small amount of scrub,gently rub it on your skin,and rinse off with water.

WARNINGS

Keep out of children

INACTIVE INGREDIENT

Aqua

INDICATIONS AND USAGE

For daily skin care

Keep out of children

PURPOSE

Reduce dark spots and enhances skin's glow